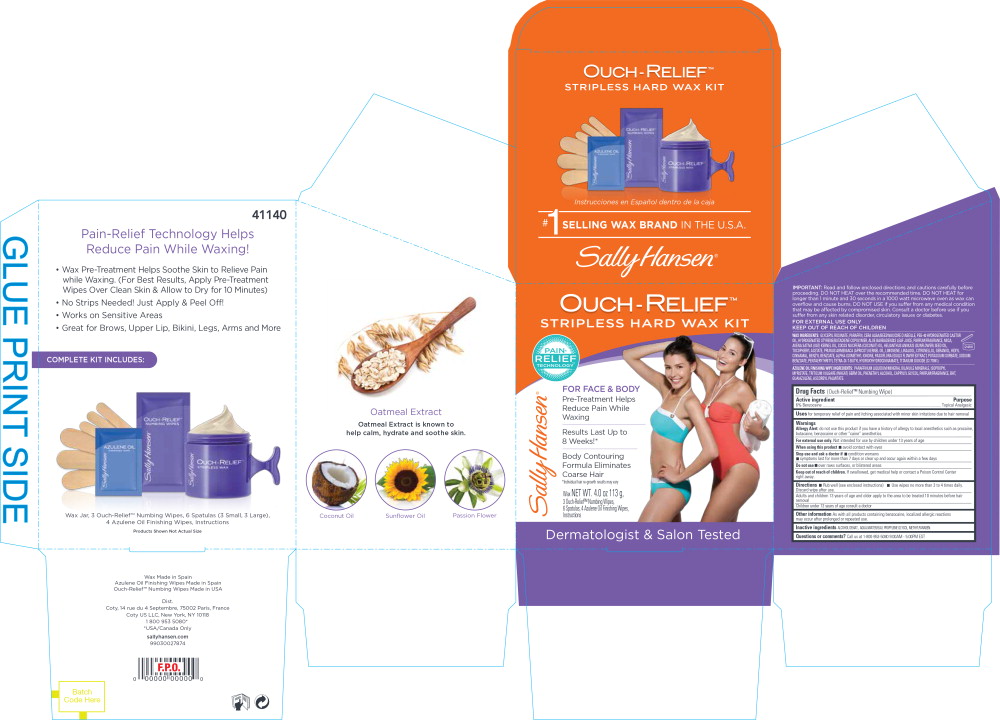 DRUG LABEL: Sally Hansen Ouch-Relief Stripless Hard Wax Kit
NDC: 66184-161 | Form: KIT | Route: TOPICAL
Manufacturer: Coty US LLC
Category: otc | Type: HUMAN OTC DRUG LABEL
Date: 20241216

ACTIVE INGREDIENTS: BENZOCAINE 6 g/1 1
INACTIVE INGREDIENTS: WATER; PROPYLENE GLYCOL; METHYLPARABEN

Sally Hansen Ouch-Relief Stripless Hard Wax Kit

(Ouch-Relief™ Numbing Wipe)

Active ingredient

6% Benzocaine

Purpose

Topical Analgesic

Uses

for temporary relief of pain and itching associated with minor skin irritations due to hair removal

Warnings

Allergy Alert:do not use this product if you have a history of allergy to local anesthetics such as procaine, butacaine, benzocaine or other “caine” anesthetics.

For external use only.Not intended for use by children under 13 years of age

When using this product

- avoid contact with eyes

Stop use and ask a doctor if

- condition worsens
- symptoms last for more than 7 days or clear up and occur again within a few days

Do not use

- over raws surfaces, or blistered areas

Keep out of reach of children.

If swallowed, get medical help or contact a Poison Control Center right away.

Directions

- Rub well (see enclosed instructions)
- Use wipes no more than 3 to 4 times daily. Discard wipe after use.

Adults and children 13 years of age and older apply to the area to be treated 10 minutes before hair removal

Children under 13 years of age consult a doctor

Other information

As with all products containing benzocaine, localized allergic reactions may occur after prolonged or repeated use.

Inactive ingredients

ALCOHOL DENAT., AQUA/WATER/EAU, PROPYLENE GLYCOL, METHYLPARABEN.

Questions or comments?

Call us at 1-800-953-5080 9:00AM - 5:00PM EST

Principal Display Panel - Sally Hansen Ouch-Relief Stripless Hard Wax Kit Label

OUCH-RELIEF™
STRIPLESS HARD WAX KIT

PAIN-
RELIEF
TECHNOLOGY™

Sally Hansen®

FOR FACE & BODY

Pre-Treatment Helps
Reduce Pain While
Waxing

Results Last Up to
8 Weeks!*

Body Contouring
Formula Eliminates
Coarse Hair

*Individual hair re-growth results may vary

Wax NET WT. 4.0 oz 113 g,

3 Ouch-Relief™ Numbing Wipes,
6 Spatulas, 4 Azulene Oil Finish Wipes,
Instructions

Dermatologist & Salon Tested